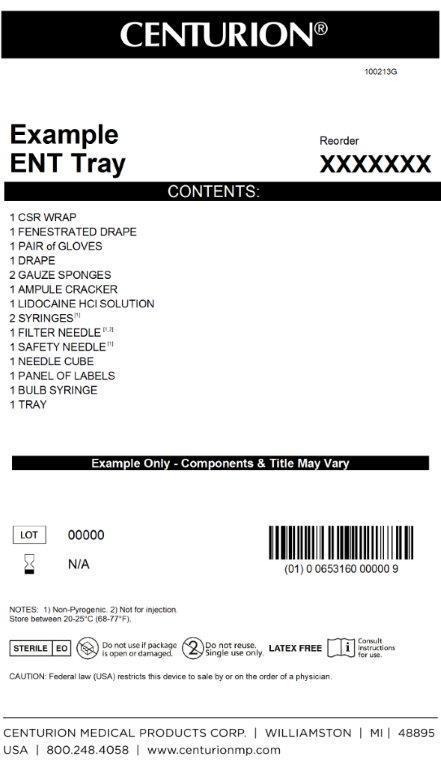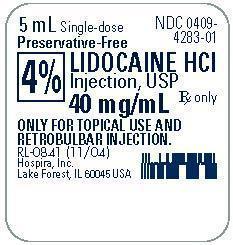 DRUG LABEL: ENT Kit
NDC: 24840-1313 | Form: KIT | Route: RETROBULBAR
Manufacturer: Centurion Medical Products
Category: other | Type: MEDICAL DEVICE
Date: 20131002

ACTIVE INGREDIENTS: LIDOCAINE HYDROCHLORIDE ANHYDROUS 40 mg/1 mL
INACTIVE INGREDIENTS: Water; SODIUM HYDROXIDE; HYDROCHLORIC ACID

ENT Kit

Description

Aqueous Solution for Topical Use

and Retrobulbar Injection

Rx only